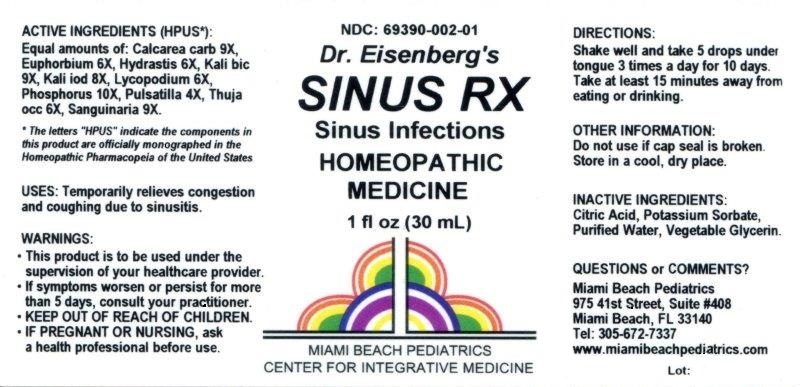 DRUG LABEL: SINUS RX
NDC: 69390-002 | Form: LIQUID
Manufacturer: Miami Beach Pediatrics pa
Category: homeopathic | Type: HUMAN OTC DRUG LABEL
Date: 20211229

ACTIVE INGREDIENTS: OYSTER SHELL CALCIUM CARBONATE, CRUDE 9 [hp_X]/1 mL; EUPHORBIA RESINIFERA RESIN 6 [hp_X]/1 mL; GOLDENSEAL 6 [hp_X]/1 mL; POTASSIUM DICHROMATE 9 [hp_X]/1 mL; POTASSIUM IODIDE 8 [hp_X]/1 mL; LYCOPODIUM CLAVATUM SPORE 6 [hp_X]/1 mL; PHOSPHORUS 10 [hp_X]/1 mL; PULSATILLA VULGARIS 4 [hp_X]/1 mL; THUJA OCCIDENTALIS LEAFY TWIG 6 [hp_X]/1 mL; SANGUINARIA CANADENSIS ROOT 9 [hp_X]/1 mL
INACTIVE INGREDIENTS: GLYCERIN; CITRIC ACID MONOHYDRATE; POTASSIUM SORBATE; WATER

Sinus RX

ACTIVE INGREDIENTS (HPUS*):

Equal amounts of: Calcarea carb 9X, Euphorbium 6X, Hydrastis 6X, Kali bic 9X, Kali iod 8X, Lycopodium 6X, Phosphorus 10X, Pulsatilla 4X, Thuja occ 6X, Sanguinaria 9X.

*The letters "HPUS" indicate the components in this product are officially monographed in the Homeopathic Pharmacopeia of the United States.

USES:

Temporarily relieves congestion and coughing due to sinusitis.

WARNINGS:

- This product is to be used under the supervision of your healthcare provider.
- If symptoms worsen or persist for more than 5 days, consult your practitioner.
- IF PREGNANT OR NURSING, ask a health professional before use.

- KEEP OUT OF REACH OF CHILDREN.

DIRECTIONS:

Shake well and take 5 drops under tongue 3 times a day for 10 days. Take at least 15 minutes away from eating or drinking.

OTHER INFORMATION:

Do not use if cap seal is broken. Store in a cool, dry place.

INACTIVE INGREDIENTS:

Citric Acid, Potassium Sorbate, Purified Water, Vegetable Glycerin.

QUESTIONS or COMMENTS?

Miami Beach Pediatrics

975 41st Street, Suite #408

Miami Beach, FL 33140

Tel: 305-672-7337

www.miamibeachpediatrics.com

PACKAGE LABEL

NDC: 69390-002-01

Dr. Eisenberg's

SINUS RX

Sinus Infections

HOMEOPATHIC MEDICINE

1 fl oz (30 mL)

MIAMI BEACH PEDIATRICS

CENTER FOR INTEGRATIVE MEDICINE

PURPOSE

Sinus Infections